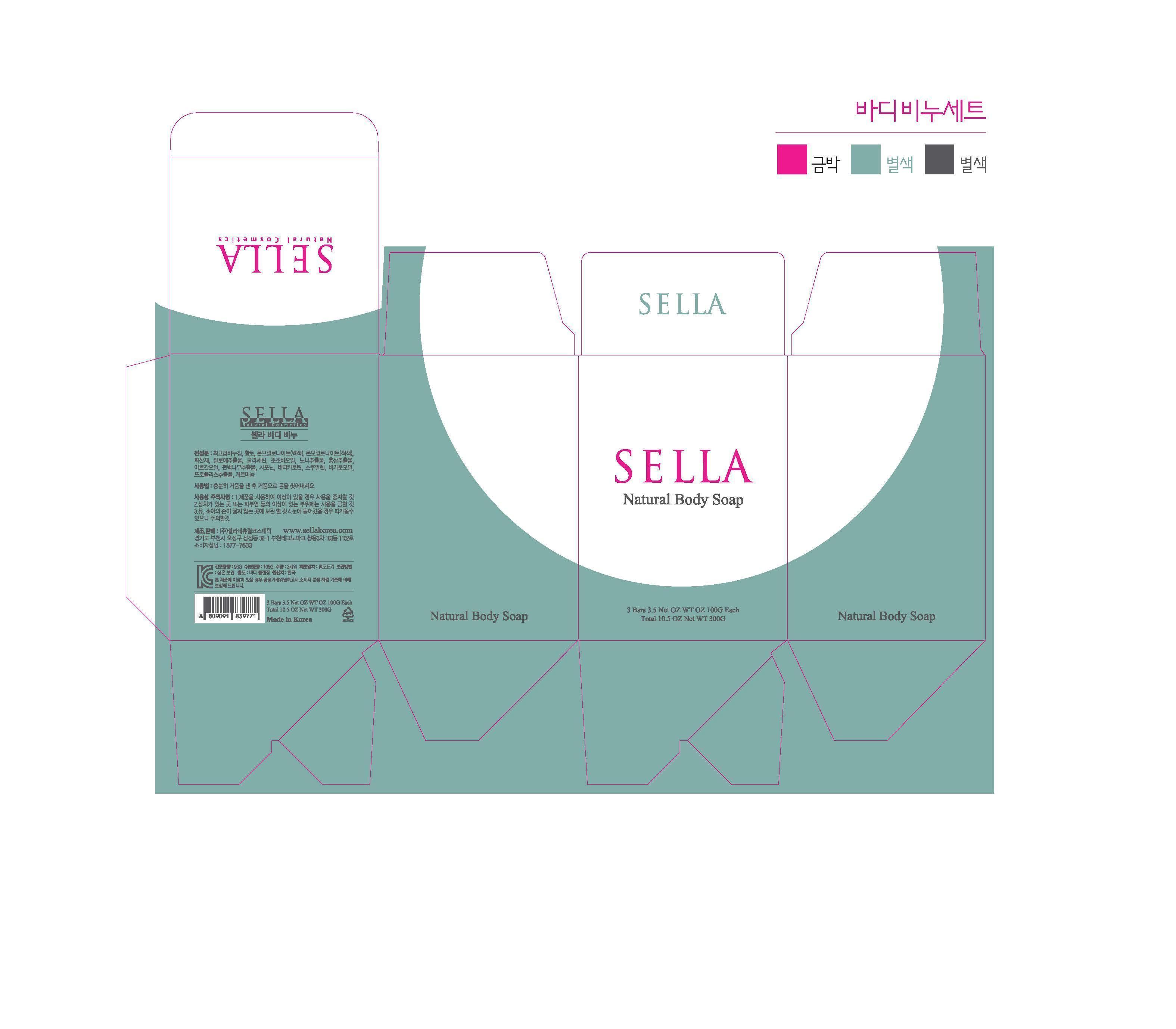 DRUG LABEL: SELLA NATURAL BODY
NDC: 69603-1001 | Form: SOAP
Manufacturer: Sella Natural Cosmetics Co.,Ltd.
Category: otc | Type: HUMAN OTC DRUG LABEL
Date: 20150211

ACTIVE INGREDIENTS: GLYCERIN 0.4 g/100 g
INACTIVE INGREDIENTS: SQUALENE; JOJOBA OIL

Drug Facts

ACTIVE INGREDIENT

glycerine

INACTIVE INGREDIENT

soap base, saponins, beta glucan, squalene, propolis ext, etc

PURPOSE

skin protectant

keep out of reach of the children

INDICATIONS AND USAGE

apply to the skin and rub gently and wash away

WARNINGS

・Stop using the product when you have skin problems or the product disagrees with your skin
・Stop using the product immediately and consult a dermatologist if you have redness, swelling, itching or irritation on the skin while or after using the product.
・Don't place the product in any place where it will be subjected to extremely high or low temperatures or direct sunlight.

DOSAGE AND ADMINISTRATION

for external use only